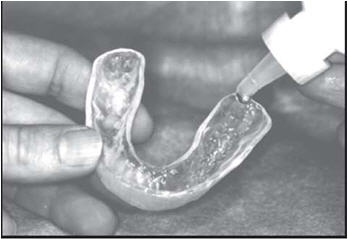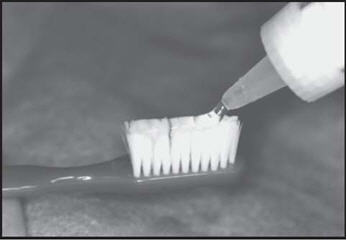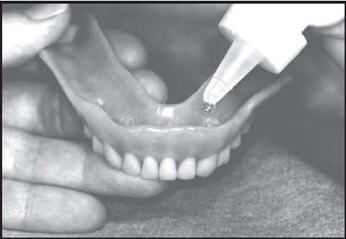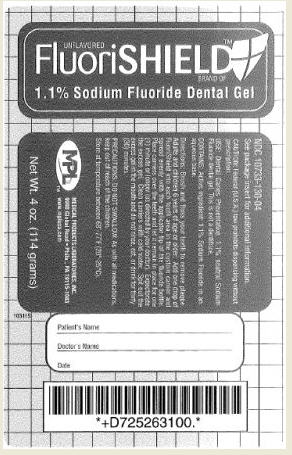 DRUG LABEL: FluoriSHIELD
NDC: 10733-130 | Form: GEL
Manufacturer: Medical Products Laboratories, Inc.
Category: prescription | Type: HUMAN PRESCRIPTION DRUG LABEL
Date: 20110211

ACTIVE INGREDIENTS: SODIUM FLUORIDE 11 mg/1 g
INACTIVE INGREDIENTS: WATER; SACCHARIN SODIUM; HYDROXYETHYL CELLULOSE (4000 MPA.S FOR 1% AQUEOUS SOLUTION)

UNFLAVORED FluoriSHIELD BRAND OF 1.1% Sodium Fluoride Dental Gel

Your dentist has selected for you FluoriShield, a 1.1% Sodium Fluoride product that was specially developed to prevent tooth decay which can occur from xerostomia (dry mouth). Dry mouth can result from radiation therapy, systemic diseases, medications which affect the salivary glands and mouth breathing. Clinical trials have shown that application of topical fluoride gel in the presence of good oral hygiene can prevent or significantly reduce tooth decay which is related to dry mouth. FluoriShield topical fluoride gel can be applied with a custom carrier or tray, directly brushed on, or used with an over denture. Your dentist will prescribe the method that is best suited for your individual needs. The gel is easily dispensed when the bottle is inverted for storing.

STORE INVERTED FOR EASY REMOVAL OF CONTENTS.

Description:

Topical neutral 1.1% sodium fluoride for use as a dental caries preventative in children and adults. This prescription product is not a dentifrice.

Warnings:

DO NOT SWALLOW. As with all medications, this product should be kept out of reach of children.

Overdose:

Accidental ingestion of a usual treatment dose (1-2mgF) is not harmful.

STORAGE AND HANDLING

Store at temperature between 68º-77ºF (20º-25ºC).

CAUTION:

Federal (U.S.A.) law prohibits dispensing without a prescription.

INSTRUCTIONS

Custom Carriers or Trays

Brush and floss your teeth to remove plaque. Adults and children 6 years of age or older: Add one drop of FluoriShield into each tooth area in the custom carrier and spread evenly with the applicator tip of the fluoride bottle. Place carriers over the teeth and let it remain in place for one (1) minute or longer (as directed by your doctor). Expectorate the excess gel. Clean carriers with cold water. Spit out the excess gel in the mouth and do not rinse, eat, or drink for thirty (30) minutes.

Brush On

Brush and floss your teeth to remove plaque. Adults and children 6 years of age or older: Apply a thin ribbon of gel to the toothbrush and spread evenly with the applicator tip of the fluoride bottle. Brush all tooth surfaces and allow fluoride to remain in place for one (1) minute or longer (as directed by your doctor). Clean carriers with cold water. Expectorate the excess gel in the mouth and do not rinse, eat, or drink for thirty (30) minutes.

Overdentures

Brush all tooth surfaces. Clean your dentures. Adults and children 6 years of age or older: Apply one (1) or two (2)drops of FluoriShield to each tooth area in your denture and place the dentures in your mouth. Leave in place for one (1) minute or longer (as directed by your doctor).Expectorate the excess gel in the mouth and do not rinse, eat, or drink for thirty (30) minutes.

™

MEDICAL PRODUCTS LABORATORIES, INC.

9990 Global Road • Phila., PA 19115-1083 800-523-0191 fax 215-677-7736 www.mplusa.com